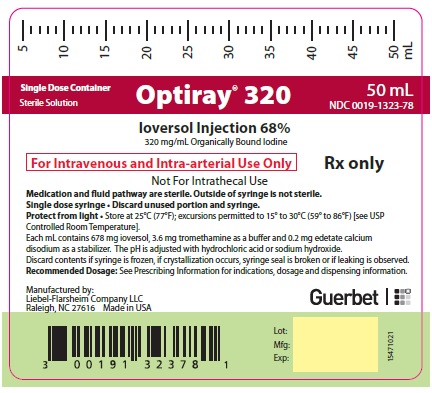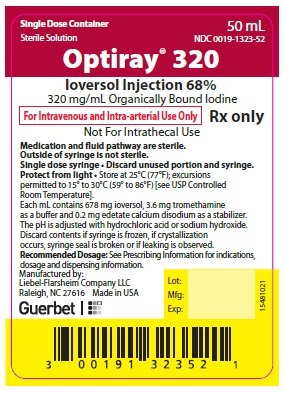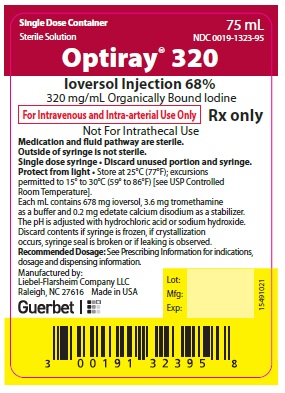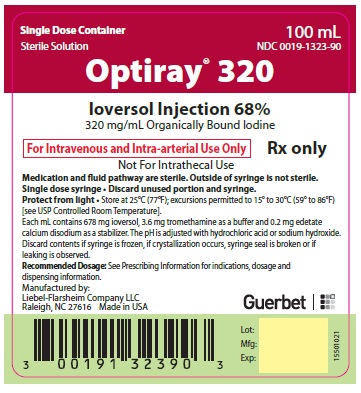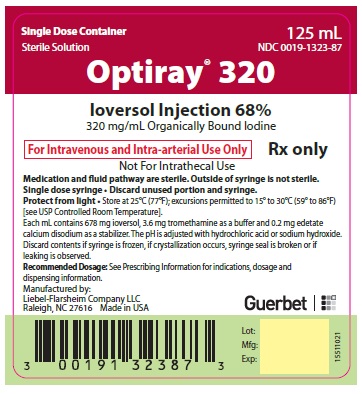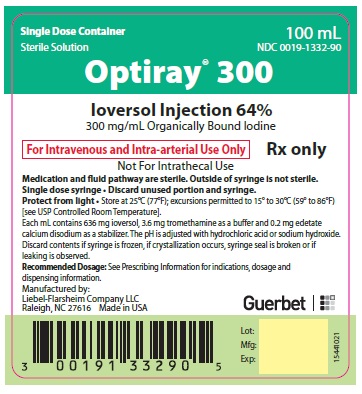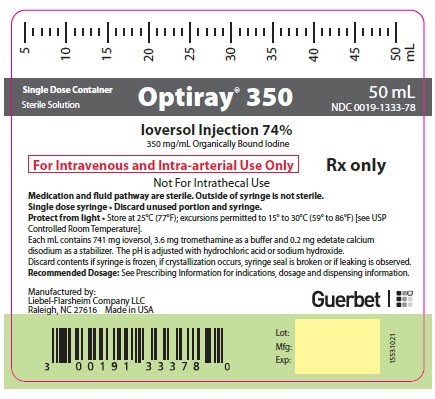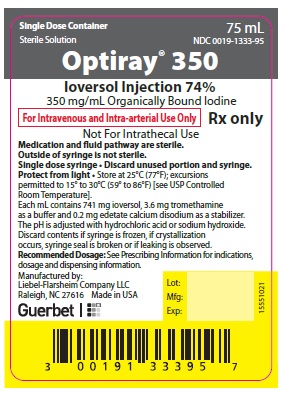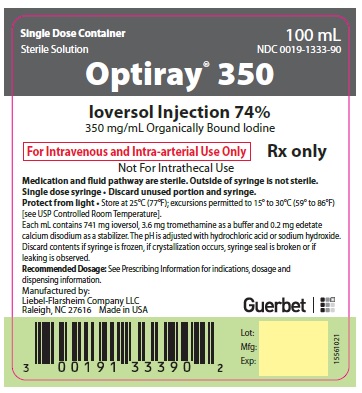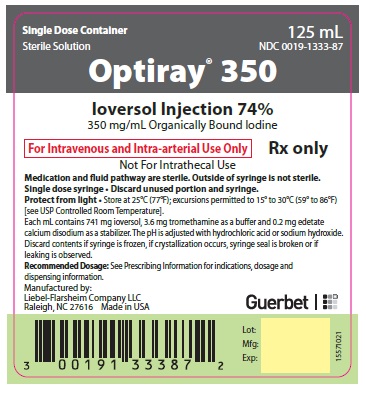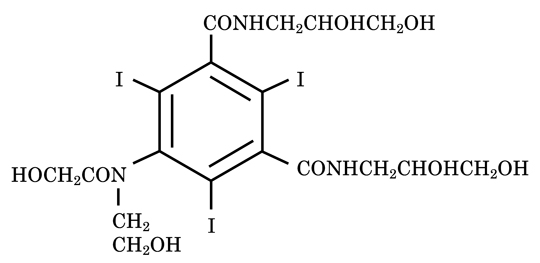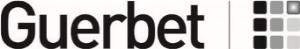 DRUG LABEL: Optiray
NDC: 0019-1333 | Form: INJECTION
Manufacturer: Liebel-Flarsheim Company LLC
Category: prescription | Type: HUMAN PRESCRIPTION DRUG LABEL
Date: 20230217

ACTIVE INGREDIENTS: IOVERSOL 741 mg/1 mL
INACTIVE INGREDIENTS: TROMETHAMINE 3.6 mg/1 mL; EDETATE CALCIUM DISODIUM 0.2 mg/1 mL; SODIUM HYDROXIDE; HYDROCHLORIC ACID

HIGHLIGHTS OF PRESCRIBING INFORMATION

These highlights do not include all the information needed to use OPTIRAY safely and effectively. See full prescribing information for OPTIRAY.
OPTIRAYTM (ioversol) injection, for intra-arterial or intra-venous use
Initial U.S. Approval: 1988

WARNING: RISKS WITH INADVERTENT INTRATHECAL ADMINISTRATION

FOR INTRA-ARTERIAL AND INTRAVENOUS USE ONLY
Inadvertent intrathecal administration may cause death, convulsions, cerebral hemorrhage, coma, paralysis, arachnoiditis, acute renal failure, cardiac arrest, seizures, rhabdomyolysis, hyperthermia, and brain edema. (5.1)

RECENT MAJOR CHANGES

Warnings and Precautions, Thyroid Dysfunction in Pediatric Patients 0 to 3 Years of Age (5.8) 2/2023

1 INDICATIONS AND USAGE

OPTIRAY is a radiographic contrast agent indicated for the following:
Intra-arterial Procedures (1.1)
Adults:

- Cerebral Arteriography (300, 320 mg iodine/mL)
- Peripheral Arteriography (300, 320, 350 mg iodine/mL)
- Visceral and Renal Arteriography, Aortography (320 mg iodine/mL)
- Coronary Arteriography and Left Ventriculography (320, 350 mg iodine/mL)

Pediatric Patients: Angiocardiography (320, 350 mg iodine/mL)

Intravenous Procedures (1.2)
Adults:

- Computed tomography (CT) Imaging of Head and Body (300, 320, 350 mg iodine/mL)
- Venography (300, 320, 350 mg iodine/mL)
- Intravenous Excretory Urography (300, 320, 350 mg iodine/mL)
- Intravenous Digital Subtraction Angiography (350 mg iodine/mL)

Pediatric Patients: CT Imaging of the Head and Body, and Intravenous Excretory Urography (320 mg iodine/mL)

2 DOSAGE AND ADMINISTRATION

Adjust the volume and concentration of OPTIRAY. Modify the dose accounting for factors such as age, body weight, vessel size, blood flow rate within the vessel. Please see details in full Prescribing Information. (2)

3 DOSAGE FORMS AND STRENGTHS

OPTIRAY (ioversol) Injection comes in three strengths: 300 mg iodine/mL (ioversol 64%), 320 mg iodine/mL (ioversol 68%), 350 mg iodine/mL (ioversol 74%) in single-dose vials, bottles, or syringes. (3)

4 CONTRAINDICATIONS

Symptomatic Hyperthyroidism (4)

5 WARNINGS AND PRECAUTIONS

- Hypersensitivity Reactions: life-threatening or fatal reactions can occur. Always have emergency equipment and trained personnel available. (5.2)
- Contrast Induced Acute Kidney Injury: Acute injury, including renal failure, can occur. Minimize dose and maintain adequate hydration to minimize risk. (5.3)
- Cardiovascular Adverse Reactions: hemodynamic disturbances including shock and cardiac arrest may occur during or after administration. (5.4)
- Thyroid Dysfunction in Pediatric Patients 0 to 3 Years of Age: Individualize thyroid function monitoring based on risk factors such as prematurity. (5.8)

6 ADVERSE REACTIONS

The most common reaction is nausea, occurring at a rate of 1 percent. (6.1)

To report SUSPECTED ADVERSE REACTIONS, contact LIEBEL-FLARSHEIM COMPANY LLC at 855-266-5037 or FDA at 1-800-FDA-1088 or www.fda.gov/medwatch.

8 USE IN SPECIFIC POPULATIONS

- Lactation: A lactating woman may pump and discard breast milk for 8 hours after OPTIRAY administration. (8.2)

FULL PRESCRIBING INFORMATION

WARNING: RISKS WITH INADVERTENT INTRATHECAL ADMINISTRATION

FOR INTRA-ARTERIAL AND INTRAVENOUS USE ONLY

Inadvertent intrathecal administration may cause death, convulsions, cerebral hemorrhage, coma, paralysis, arachnoiditis, acute renal failure, cardiac arrest, seizures, rhabdomyolysis, hyperthermia, and brain edema. [see Warnings and Precautions (5.1)]

1 INDICATIONS AND USAGE

OPTIRAY is indicated for:

1.1 Intra-arterial

In adults

- OPTIRAY 300: cerebral arteriography and peripheral arteriography.
- OPTIRAY 320: cerebral arteriography, peripheral arteriography, visceral and renal arteriography, aortography, coronary arteriography, and left ventriculography.
- OPTIRAY 350: peripheral arteriography coronary arteriography, and left ventriculography.

In pediatric patients

- OPTIRAY 320 and OPTIRAY 350: angiocardiography.

1.2 Intra-venous

In adults

- OPTIRAY 300: CT imaging of the head and body, venography, and intravenous excretory urography.
- OPTIRAY 320: CT imaging of the head and body, venography, and intravenous excretory urography.
- OPTIRAY 350: CT imaging of the head and body, venography, intravenous excretory urography, and intravenous digital subtraction angiography (IV-DSA).

- In pediatric patients OPTIRAY 320: CT imaging of the head and body, and intravenous excretory urography.

2 DOSAGE AND ADMINISTRATION

2.1 Important Administration Instructions

- OPTIRAY is for intravascular use only [see Boxed Warning, Contraindications (4), Warnings and Precautions (5.1)].
- Use sterile technique for all handling and administration of OPTIRAY.
- Inspect glass and plastic containers prior to use for breakage or other damage and do not use damaged containers.
- Warm OPTIRAY and administer at body or room temperature.
- Inspect OPTIRAY for particulate matter or discoloration before administration. Do not administer if OPTIRAY contains particulate matter or is discolored.
- Do not mix OPTIRAY with other drugs, solutions or total parenteral nutrition mixtures.
- Use the lowest dose necessary to obtain adequate visualization.
- Adjust the volume and concentration of OPTIRAY. Modify the dose accounting for factors such as age, body weight, vessel size, blood flow rate within the vessel, anticipated pathology, degree and extent of opacification required, structure(s) or area to be examined, disease processes affecting the patient, and equipment and technique to be employed.
- Avoid extravasation when injecting OPTIRAY; especially in patients with severe arterial or venous disease [see Warnings and Precautions (5.6)].
- Hydrate patients before and after OPTIRAY administration [see Warnings and Precautions (5.3)].
- Discard unused portion of OPTIRAY from single-dose container after use.

2.2 Radio Frequency Identification (RFID)-Tagged Syringe Directions for Use

- The RFID-tagged syringe must be used with an Optivantage Injector with RFID technology [see How Supplied/Storage and Handling (16.2)]. The RFID tag allows for the exchange of product information such as lot number, expiration, concentration, and identification of the syringe as being “unused” prior to use and “used” after product administration.
- Do not operate any part of the Optivantage Injector System and RFID-tagged syringes within 6 inches (15 cm) of a pacemaker and/or defibrillator.
- If the RFID tag is damaged or otherwise non-functional, the OPTIRAY syringe with the non-functional RFID tag may still be used; however, no data will be transferred to the injector.

2.3 Intra-arterial Procedures in Adults

Cerebral Arteriography

Use OPTIRAY 300 or OPTIRAY 320. The recommended dose for visualization of cerebral arteries is shown below (may repeat as necessary):

Diagnostic area | Dose | Maximum Cumulative Dose
carotid or vertebral arteries | 2 mL to 12 mL | 200 mL
aortic arch injection (four vessel study) | 20 mL to 50 mL | 200 mL

- Peripheral Arteriography

Use OPTIRAY 300, OPTIRAY 320 or OPTIRAY 350. The recommended dose for visualization of peripheral arteries is shown below (may repeat as necessary):

Diagnostic area | Dose | Maximum Cumulative Dose
aorta-iliac runoff | 60 mL (range 20 mL to 90 mL) | 250 mL
common iliac, femoral | 40 mL (range 10 mL to 50 mL) | 250 mL
subclavian, brachial | 20 mL (range 15 mL to 30 mL) | 250 mL

- Visceral and Renal Arteriography and Aortography

Use OPTIRAY 320. The recommended dose for visualization for the aorta and visceral arteries is shown below (may repeat as necessary):

Diagnostic area | Dose | Maximum Cumulative Dose
aorta | 45 mL (range 10 mL to 80 mL) | 250 mL
celiac | 45 mL (range 12 mL to 60 mL) | 250 mL
superior mesenteric | 45 mL (range 15 mL to 60 mL) | 250 mL
renal or inferior mesenteric | 9 mL (range 6 mL to 15 mL) | 250 mL

- Coronary Arteriography and Left Ventriculography

Use OPTIRAY 320 or OPTIRAY 350. The recommended dose for visualization of the coronary arteries and left ventricle is shown below (may repeat as necessary):

Diagnostic area | Dose | Maximum Cumulative Dose
left coronary | 8 mL (range 2 mL to 10 mL) | 250 mL
right coronary | 6 mL (range 1 mL to 10 mL) | 250 mL
left ventricle | 40 mL (range 30 mL to 50 mL) | 250 mL

2.4 Intravenous Procedures in Adults

- Computed Tomography

Use OPTIRAY 300, OPTIRAY 320, or OPTIRAY 350 for head and body imaging.

Head Imaging
The recommended dosing is shown below:

- Scan immediately after completion of the intravenous administration.

 | Infusion
OPTIRAY 300 | 50 mL to 150 mL
OPTIRAY 320 | 50 mL to 150 mL
OPTIRAY 350 | 50 mL to 150 mL

Body Imaging
OPTIRAY may be administered by bolus injection, by rapid infusion, or by a combination of both. The recommended dosing is shown below:

- Scanning interval will vary with indication and target organ.

 | Bolus Injection | Infusion
OPTIRAY 300 | 25 mL to 75 mL | 50 mL to 150 mL
OPTIRAY 320 | 25 mL to 75 mL | 50 mL to 150 mL
OPTIRAY 350 | 25 mL to 75 mL | 50 mL to 150 mL

- Venography

Use OPTIRAY 300, OPTIRAY 320 or OPTIRAY 350. The recommended dose is 50 mL to 100 mL per extremity; with a maximum cumulative dose of 250 mL.

- Intravenous Urography

Use OPTIRAY 350, OPTIRAY 320, or OPTIRAY 300. The recommended dose is shown below:

 | Usual Dose | High Dose Urography | Maximum Dose
OPTIRAY 300 | 50 mL to 75 mL | 1.6 mL/kg | 150 mL
OPTIRAY 320 | 50 mL to 75 mL | 1.5 mL/kg to 2 mL/kg | 150 mL
OPTIRAY 350 | 50 mL to 75 mL | 1.4 mL/kg | 140 mL

- Intravenous Digital Subtraction Angiography (IV-DSA)

Use OPTIRAY 350. The recommended dose range per injection is 30 mL to 50 mL; may repeat as necessary with a maximum cumulative dose of 250 mL.

Injection rates will vary depending on the site of catheter placement and vessel size.

- Central catheter injections are usually made at a rate of between 10 mL/second and 30 mL/second.
- Peripheral injections are usually made at a rate of between 12 mL/second and 20 mL/second.

2.5 Pediatric Dosing

Intra-arterial Procedures

- Angiocardiography

Use OPTIRAY 350 or OPTIRAY 320. The recommended single ventricular dose is 1.25 mL/kg (range 1 mL/kg to 1.5 mL/kg). The maximum cumulative dose is 5 mL/kg up to a maximum total volume of 250 mL.

Intravenous Procedures

- Computed Tomography

Use OPTIRAY 320.

Head and Body Imaging
The recommended dose in pediatric patients is 1.5 mL/kg to 2 mL/kg (range 1 mL/kg to 3 mL/kg).

- Intravenous Urography

Use OPTIRAY 320. The recommended dose for pediatric patients is 1 mL/kg to 1.5 mL/kg (range 0.5 mL/kg to 3 mL/kg); with a maximum cumulative dose not exceeding 3 mL/kg.

3 DOSAGE FORMS AND STRENGTHS

Injection: clear, colorless to pale yellow solutions containing no undissolved solids, available in the following strengths and single-dose containers:

Imaging Product | mg of ioversol per mL | mg of organically boundiodine; per mL | Presentations
Imaging Product | mg of ioversol per mL | mg of organically boundiodine; per mL | Vials | Bottles | Hand-held syringes | Power injector syringes
OPTIRAY 300; (Ioversol 64%) | 636 | 300 | No | Yes | Yes | Yes
OPTIRAY 320; (Ioversol 68%) | 678 | 320 | Yes | Yes | Yes | Yes
OPTIRAY 350; (Ioversol 74%) | 741 | 350 | No | Yes | Yes | Yes

4 CONTRAINDICATIONS

Symptomatic Hyperthyroidism

5 WARNINGS AND PRECAUTIONS

5.1 Risks Associated with Inadvertent Intrathecal Administration

OPTIRAY is indicated for intravascular use only [see Dosage and Administration (2.1)]. Inadvertent intrathecal administration can cause death, convulsions, cerebral hemorrhage, coma, paralysis, arachnoiditis, acute renal failure, cardiac arrest, seizures, rhabdomyolysis, hyperthermia, and brain edema.

5.2 Hypersensitivity Reactions

OPTIRAY can cause life-threatening or fatal hypersensitivity reactions including anaphylaxis and anaphylactic shock. Manifestations include respiratory arrest, laryngospasm, bronchospasm, angioedema, and shock. Most severe reactions develop shortly after the start of the injection (e.g. within 1 to 3 minutes), but delayed reactions may occur. There is an increased risk in patients with a history of a previous reaction to contrast agent, and known allergies (i.e., bronchial asthma, drug, or food allergies), and other hypersensitivities. Premedication with antihistamines or corticosteroids to avoid or minimize possible allergic reactions does not prevent serious life-threatening reactions, but may reduce both their incidence and severity.

Obtain a history of allergy, hypersensitivity, or prior hypersensitivity reactions to iodinated contrast agents. Always have emergency resuscitation equipment and trained personnel available and monitor all patients for hypersensitivity reactions.

5.3 Contrast Induced Acute Kidney Injury

Acute kidney injury, including renal failure, may occur after OPTIRAY administration. Risk factors include: pre-existing renal impairment, dehydration, diabetes mellitus, congestive heart failure, advanced vascular disease, elderly age, concomitant use of nephrotoxic or diuretic medications, multiple myeloma / paraproteinaceous diseases, repetitive and/or large doses of an iodinated contrast agent.

Use the lowest necessary dose of OPTIRAY in patients with renal impairment. Adequately hydrate patients prior to and following OPTIRAY administration. Do not use laxatives, diuretics, or preparatory dehydration prior to OPTIRAY administration.

5.4 Cardiovascular Adverse Reactions

OPTIRAY increases the circulatory osmotic load and may induce acute or delayed hemodynamic disturbances in patients with congestive heart failure, severely impaired renal function, combined renal and hepatic disease, combined renal and cardiac disease, particularly when repetitive or large doses are administered.

Life-threatening or fatal cardiovascular reactions have occurred with the use of OPTIRAY, including cardiac arrest, hypotensive collapse, and shock. Most deaths occur within 10 minutes of injection; with cardiovascular disease as the main underlying factor. Cardiac decompensation, serious arrhythmias, and myocardial ischemia or infarction can occur during coronary arteriography and ventriculography.

Based upon literature reports, deaths from the administration of iodinated contrast agents range from 6.6 per 1 million (0.00066 percent) to 1 in 10,000 patients (0.01 percent). Use the lowest necessary dose of OPTIRAY in patients with congestive heart failure and always have emergency resuscitation equipment and trained personnel available. Monitor all patients for severe cardiovascular reactions.

5.5 Thromboembolic Events

Angiocardiography
Serious, fatal, thromboembolic events causing myocardial infarction and stroke can occur during angiographic procedures with OPTIRAY. During these procedures, increased thrombosis and activation of the complement system occurs. Risk factors for thromboembolic events include: length of procedure, catheter and syringe material, underlying disease state, and concomitant medications.

To minimize thromboembolic events use meticulous angiographic technique. Avoid blood remaining in contact with syringes containing OPTIRAY, which increases the risk of clotting. Avoid angiocardiography in patients with homocystinuria because of the risk of inducing thrombosis and embolism [see Clinical Pharmacology (12.2)].

5.6 Extravasation and Injection Site Reactions

Extravasation can occur with OPTIRAY administration, particularly in patients with severe arterial or venous disease and can be associated with pain, hemorrhage and necrosis. Ensure intravascular placement of catheters prior to injection. Monitor patients for extravasation and advise patients to seek medical care for progression of symptoms.

5.7 Thyroid Storm in Patients with Hyperthyroidism

OPTIRAY is contraindicated in patients with symptomatic hyperthyroidism [see Contraindications (4)]. Thyroid storm has occurred following the intravascular use of iodinated radiopaque agents in patients with hyperthyroidism or with an autonomously functioning thyroid nodule. Evaluate the risk in such patients before use of OPTIRAY.

5.8 Thyroid Dysfunction in Pediatric Patients 0 to 3 Years of Age

Thyroid dysfunction characterized by hypothyroidism or transient thyroid suppression has been reported after both single exposure and multiple exposures to iodinated contrast media (ICM) in pediatric patients 0 to 3 years of age.

Younger age, very low birth weight, prematurity, underlying medical conditions affecting thyroid function, admission to neonatal or pediatric intensive care units, and congenital cardiac conditions are associated with an increased risk of hypothyroidism after ICM exposure. Pediatric patients with congenital cardiac conditions may be at the greatest risk given that they often require high doses of contrast during invasive cardiac procedures.

An underactive thyroid during early life may be harmful for cognitive and neurological development and may require thyroid hormone replacement therapy. After exposure to ICM, individualize thyroid function monitoring based on underlying risk factors, especially in term and preterm neonates.

5.9 Hypertensive Crisis in Patients with Pheochromocytoma

Hypertensive crisis has occurred after the use of iodinated radiopaque contrast agents in patient with pheochromocytoma. Closely monitor patients when administering OPTIRAY if pheochromocytoma or catecholamine-secreting paraganglioma is suspected. Inject the minimum amount of OPTIRAY necessary and have measures for treatment of hypertensive crisis readily available.

5.10 Sickle Cell Crisis in Patients with Sickle Cell Disease

Iodinated contrast agents may promote sickling in individuals who are homozygous for sickle cell disease. Hydrate patients prior to and following OPTIRAY administration, use OPTIRAY only if the necessary imaging information cannot be obtained with alternative imaging modalities, and inject the minimum amount necessary.

5.11 Severe Cutaneous Adverse Reactions

Severe cutaneous adverse reactions (SCAR) may develop from 1 hour to several weeks after intravascular contrast agent administration. These reactions include Stevens-Johnson syndrome and toxic epidermal necrolysis (SJS/TEN), acute generalized exanthematous pustulosis (AGEP) and drug reaction with eosinophilia and systemic symptoms (DRESS). Reaction severity may increase and time to onset may decrease with repeat administration of a contrast agent; prophylactic medications may not prevent or mitigate severe cutaneous adverse reactions. Avoid administering OPTIRAY to patients with a history of a severe cutaneous adverse reaction to OPTIRAY.

6 ADVERSE REACTIONS

The following clinically significant adverse reactions are described elsewhere in the labeling:

- Risks Associated with Inadvertent Intrathecal Administration [see Warnings and Precautions (5.1)]
- Hypersensitivity Reactions [see Warnings and Precautions (5.2)]
- Contrast Induced Acute Kidney Injury [see Warnings and Precautions (5.3)]
- Cardiovascular Adverse Reactions [see Warnings and Precautions (5.4)]
- Thromboembolic Events [see Warnings and Precautions (5.5)]
- Thyroid Dysfunction in Pediatric Patients 0 to 3 Years of Age [see Warnings and Precautions (5.8)]
- Severe Cutaneous Adverse Reactions [see Warnings and Precautions (5.11)]

6.1 Clinical Trials Experience

Adult Patients
Because clinical trials are conducted under widely varying conditions, adverse reaction rates observed in the clinical trials of a drug cannot be directly compared to rates in the clinical trials of another drug and may not reflect the rates observed in practice.

The following listing shows adverse reactions based upon clinical trials with OPTIRAY (ioversol) in 4,187 patients. Adverse reactions are listed by organ system according to clinical importance. More severe reactions are listed before others in a system regardless of incidence. The most common reaction is nausea, occurring at a rate of 1 percent.

Cardiac disorders
Cardiac arrest, myocardial infarction, arrhythmia, atrioventricular block complete, atrioventricular block, nodal rhythm, bradycardia, angina pectoris, palpitations

Ear and labyrinth disorders
Vertigo, tinnitus

Eye disorders
Vision blurred, periorbital edema, conjunctivitis

Gastrointestinal disorders
Nausea, vomiting, abdominal pain, dysphagia, dry mouth

General disorders and administration site conditions
Chest pain, pain, injection site pain, injection site hematoma, extravasation, pyrexia, swelling, asthenia, malaise, fatigue, chills

Infections and infestations
Rhinitis

Injury, poisoning, and procedural complications
Heart injury, vascular pseudoaneurysm

Investigations
Electrocardiogram ST segment depression, blood pressure decreased

Metabolism and nutrition disorders
Acidosis

Musculoskeletal and connective tissue disorders
Muscular weakness, muscle spasms, back pain

Nervous system disorders
Cerebral infarction, aphasia, tremor, dizziness, presyncope, headache, paraesthesia, dysgeusia

Psychiatric disorders
Hallucination, visual hallucination, disorientation, anxiety

Renal and urinary disorders
Urinary retention, renal pain, polyuria

Respiratory, thoracic, and mediastinal disorders
Laryngeal edema, hypoxia, pulmonary edema, dyspnea, hyperventilation, cough, sneezing, nasal congestion

Skin and subcutaneous tissue disorders
Urticaria, rash, pruritus, swelling face, hyperhidrosis, erythema

Vascular disorders
Hypertension, hypotension, arterial spasm, vasospasm, vasodilation, flushing

Pediatric Patients
In clinical studies involving 311 patients for pediatric angiocardiography, contrast enhanced computed tomographic imaging of the head and body, and intravenous excretory urography; 6% of patients reported an adverse reaction, with the most common adverse reactions being nausea and fever. Adverse reactions reported were similar in quality and frequency to the adverse events reported by adults.

6.2 Postmarketing Experience

The following additional adverse drug reactions have been reported during post-approval use of OPTIRAY. Because these reactions are reported voluntarily from a population of uncertain size, it is not always possible to reliably estimate frequency or establish a causal relationship to drug exposure.

Cardiac disorders: coronary artery spasm, cyanosis, arrhythmia (ventricular fibrillation, tachycardia, extrasystole), ECG abnormal.

Endocrine disorders: hyperthyroidism, hypothyroidism.

Eye disorders: temporary blindness, conjunctivitis (including eye irritation, ocular hyperemia, watery eyes).

Gastrointestinal disorders: tongue edema, salivary hypersecretion.

General disorders and administration site conditions: injection site reactions including pain, hemorrhage, and necrosis especially after extravasation [see Warnings and Precautions (5.6)], face edema, feeling hot.

Immune system disorders: hypersensitivity reactions including fatal anaphylactic shock.

Nervous system disorders: seizure, loss of consciousness, somnolence, hypoesthesia, dyskinesia, amnesia.

Respiratory disorders: Respiratory arrest, asthma, bronchospasm, laryngeal spasm and obstruction, throat irritation, dysphonia.

Skin and subcutaneous tissue disorders: Reactions range from mild (e.g. rash, erythema, pruritus, urticaria, and skin discoloration) to severe: [e.g. Stevens-Johnson syndrome and toxic epidermal necrolysis (SJS/TEN)], acute generalized exanthematous pustulosis (AGEP) and drug reaction with eosinophilia and systemic symptoms (DRESS).

Vascular Disorders: phlebitis, thrombosis.

7 DRUG INTERACTIONS

7.1 Drug-Drug Interactions

Metformin

In patients with renal impairment, metformin can cause lactic acidosis. Iodinated contrast agents appear to increase the risk of metformin induced lactic acidosis, possibly as a result of worsening renal function. Stop metformin at the time of, or prior to, OPTIRAY administration in patients with an eGFR between 30 and 60 mL/min/1.73 m^2; in patients with a history of hepatic impairment, alcoholism or heart failure; or in patients who will be administered intra-arterial iodinated contrast agents. Re-evaluate eGFR 48 hours after the imaging procedure, and reinstitute only after renal function is stable.

Radioactive Iodine

Administration of iodinated contrast agents may interfere with thyroid uptake of radioactive iodine (I 131) and decrease therapeutic efficacy in patients with carcinoma of the thyroid. The decrease in efficacy lasts for 6-8 weeks.

Oral Cholecystographic Contrast Agents

Renal toxicity has been reported in patients with liver impairment who were given oral cholecystographic agents followed by intravascular contrast agents. Administration of OPTIRAY should be postponed in patients who have recently received a cholecystographic contrast agent.

7.2 Drug/Laboratory Test Interactions

- Protein-Bound Iodine, Radioactive Iodine Determinations

The results of protein bound iodine and radioactive iodine uptake studies, which depend on iodine estimation, will not accurately reflect thyroid function for up to 16 days following administration of iodinated contrast agent. However, thyroid function tests that do not depend on iodine estimations, e.g., T3 resin uptake and total or free thyroxine (T4) assays are not affected.

8 USE IN SPECIFIC POPULATIONS

8.1 Pregnancy

Risk Summary

Postmarketing data with OPTIRAY use in pregnant women are insufficient to determine if there is a risk of drug-associated adverse developmental outcomes. Ioversol crosses the placenta and reaches fetal tissues in small amounts [see Data]. In animal reproduction studies, no adverse developmental effects were observed following daily intravenous administrations of ioversol to pregnant rats (from Gestation Day 7 to 17) and rabbits (Gestation Day 6 to 18) at doses 0.35 and 0.71 times, respectively, the maximum recommended human dose.

The estimated background risk of major birth defects and miscarriage for the indicated population is unknown. All pregnancies have a background risk of major birth defects, loss, or other adverse outcomes. In the U.S. general population, the estimated background risk of major birth defects and miscarriages in clinically recognized pregnancies is 2-4% and 15-20%, respectively.

Data

Human Data

Literature reports show that ioversol crosses the placenta and is visualized in the digestive tract of exposed infants after birth.

Animal Data
Developmental toxicity studies were conducted with ioversol given intravenously at doses of 0, 0.2, 0.8, and 3.2 g iodine/kg/day from Gestation Day 7 to 17 and 6 to 18, in rats and rabbits, respectively. No adverse effects on embryo-fetal development were observed in either species at the maximum dose tested (3.2 g iodine/kg/day). Maternal toxicity was observed in rabbits at 0.8 and 3.2 g iodine/kg/day.

8.2 Lactation

Risk Summary

There is no information about the presence of ioversol in human or animal milk, the effects of the drug on the breastfed infant, or the effects of the drug on milk production. However, iodinated contrast agents are excreted unchanged in human milk in very low amounts with poor absorption from the gastrointestinal tract of the breastfed infant. The developmental and health benefits of breastfeeding should be considered along with the mother’s clinical need for OPTIRAY and any potential adverse effects on the breastfed infant from OPTIRAY or from the underlying maternal condition.

Clinical Considerations

Interruption of breastfeeding after exposure to iodinated contrast agents is not necessary because the potential exposure of the breastfed infant to iodine is small. However, a lactating woman may consider interrupting breastfeeding and pumping and discarding breast milk for 8 hours (approximately 5 elimination half-lives) after OPTIRAY administration in order to minimize drug exposure to a breast fed infant.

8.4 Pediatric Use

Safety and effectiveness in pediatric patients have been established for the use of OPTIRAY 350 and OPTIRAY 320 in angiocardiography; and for OPTIRAY 320 in computed tomographic imaging of the head and body, and intravenous excretory urography. Use of OPTIRAY 350 and OPTIRAY 320 in these age groups is based on controlled clinical trials involving 159 patients for pediatric angiocardiography; computed tomographic imaging of the head and body, and intravenous excretory urography. In general, the types of adverse reactions reported are similar to those of adults [see Adverse Reactions (6.1)].

Safety and effectiveness of OPTIRAY 300 has not been established in pediatric patients.

Pediatric patients at higher risk of experiencing adverse reactions to OPTIRAY include patients with: asthma, sensitivity to medication and/or allergens, congestive heart failure, serum creatinine greater than 1.5 mg/dL, or age less than 12 months. Thyroid function tests indicative of hypothyroidism or transient thyroid suppression have been uncommonly reported following iodinated contrast media administration in pediatric patients, including infants. Some patients were treated for hypothyroidism [See Adverse Reactions (6.2)].

Thyroid function tests indicative of thyroid dysfunction, characterized by hypothyroidism or transient thyroid suppression have been uncommonly reported following iodinated contrast media administration in pediatric patients, including term and preterm neonates; some patients were treated for hypothyroidism. After exposure to iodinated contrast media, individualize thyroid function monitoring in pediatric patients 0 to 3 years of age based on underlying risk factors, especially in term and preterm neonates [see Warnings and Precautions (5.8) and Adverse Reactions (6.2)].

8.5 Geriatric Use

Ioversol is nearly completely excreted as parent drug by the kidney, and the risk of adverse reactions to OPTIRAY may be greater in patients with impaired renal function. Because elderly patients are more likely to have decreased renal function, dose selection should be cautious usually starting at the low end of the dosing range, reflecting the greater frequency of decreased hepatic, renal or cardiac function, and of concomitant disease or other drug therapy.

8.6 Renal Impairment

Ioversol is nearly completely excreted as parent drug by the kidney and renal impairment is expected to reduce the rate of elimination. Ioversol can be removed by dialysis.

10 OVERDOSAGE

The adverse effects of overdosage are life-threatening and affect mainly the pulmonary and cardiovascular system. Treatment of an overdosage is directed toward the support of all vital functions and prompt institution of symptomatic therapy.

Ioversol does not bind to plasma or serum protein and is, therefore, dialyzable.

11 DESCRIPTION

11.1 Chemical Characteristics

OPTIRAY (ioversol injection) is a non-ionic radiographic contrast agent. OPTIRAY formulations are sterile, nonpyrogenic, aqueous solutions intended for intravascular use. Ioversol is designated chemically as N,N'-Bis (2,3-dihydroxypropyl)-5-[N-(2-hydroxyethyl) -glycolamido] -2,4,6-triiodoisophthalamide. The molecular weight of ioversol is 807.11 and the organically bound iodine content is 47.2%.

The structural formula of ioversol is as follows:

OPTIRAY is available in three strengths:

- OPTIRAY 300 (ioversol injection 64%): Each mL contains 300 mg organically bound iodine, 636 mg ioversol, 3.6 mg, tromethamine, 0.2 mg edetate calcium disodium.
- OPTIRAY 320 (ioversol injection 68%): Each mL contains 320 mg organically bound iodine, 678 mg of ioversol, 3.6 mg tromethamine, 0.2 mg edetate calcium disodium.
- OPTIRAY 350 (ioversol injection 74%): Each mL contains 350 mg organically bound iodine, 741 mg ioversol, 3.6 mg tromethamine, 0.2 mg edetate calcium disodium.

The pH of the OPTIRAY formulations is adjusted to 6.0 to 7.4 with hydrochloric acid or sodium hydroxide. All solutions are sterilized by autoclaving and contain no preservatives. Ioversol does not dissociate in solution.

11.2 Physical Characteristics

Some physical and chemical properties of these formulations are listed below:

 | OPTIRAY 300 | OPTIRAY 320 | OPTIRAY 350
Ioversol content; (mg/mL) | 636 | 678 | 741
Iodine content (mg I/mL) | 300 | 320 | 350
Osmolality (mOsm/kg water) | 651 | 702 | 792
Viscosity (cps)
at 25°C | 8.2 | 9.9 | 14.3
at 37°C | 5.5 | 5.8 | 9.0
Specific Gravity; at 37°C | 1.352 | 1.371 | 1.405

The OPTIRAY formulations are clear, colorless to pale yellow solutions containing no undissolved solids. Crystallization does not occur at room temperature. OPTIRAY solutions have osmolalities 1.8 to 2.8 times that of plasma (285 mOsm/kg water) as shown in the above table and are hypertonic under conditions of use.

12 CLINICAL PHARMACOLOGY

12.1 Mechanism of Action

Intravascular injection of ioversol opacifies vessels in the path of the flow of the contrast medium, permitting visualization of the internal structures until significant hemodilution occurs.

In imaging of the body, iodinated contrast agents diffuse from the vascular into the extravascular space. In normal brain with an intact blood-brain barrier, contrast does not diffuse into the extravascular space. In patients with a disrupted blood-brain barrier, contrast agent accumulates in the interstitial space in the region of disruption.

12.2 Pharmacodynamics

Following administration of OPTIRAY, the degree of enhancement is directly related to the iodine content in an administered dose. Peak iodine plasma levels occur immediately following rapid injection. The time to maximum contrast enhancement can vary, depending on the organ, from the time that peak blood iodine concentrations are reached to one hour after intravenous bolus administration. When a delay between peak blood iodine concentrations and peak contrast is present, it suggests that radiographic contrast enhancement is at least in part dependent on the accumulation of iodine-containing medium within the lesion and outside the blood pool.

For angiography, contrast enhancement is greatest immediately (15 seconds to 120 seconds) after rapid injection. Iodinated contrast agents may be visualized in the renal parenchyma within 30-60 seconds following rapid intravenous injection. Opacification of the calyces and pelves in patients with normal renal function becomes apparent within 1-3 minutes, with optimum contrast occurring within 5-15 minutes.

12.3 Pharmacokinetics

In 12 healthy volunteers (6 receiving 50 mL and 6 receiving 150 mL of OPTIRAY 320), elimination half-life was 1.5 hours for both doses.

Distribution
In an in vitro human plasma study, ioversol did not bind to protein. The volume of distribution in adults was 0.26 L/kg body weight, consistent with distribution to the extracellular space.

Elimination
Metabolism
Ioversol does not undergo significant metabolism, deiodination or biotransformation.

Excretion
Greater than 95% of the administered dose was excreted in urine within the first 24 hours, with the peak urine concentration occurring in the first two hours after administration.

13 NONCLINICAL TOXICOLOGY

13.1 Carcinogenesis, Mutagenesis, Impairment of Fertility

No long term animal studies have been performed to evaluate carcinogenic potential. Nonclinical studies show that ioversol is not mutagenic and does not affect fertility.

13.2 Animal Toxicology and/or Pharmacology

Animal studies indicate that ioversol does not cross the blood-brain barrier.

16 HOW SUPPLIED/STORAGE AND HANDLING

16.1 How Supplied

OPTIRAY is a clear, colorless to pale yellow, sterile, pyrogen-free, aqueous solution available in three strengths. The products are supplied in containers from which the air has been displaced by nitrogen. OPTIRAY is supplied in the following single-dose configurations:

OPTIRAY 350 | NDC Number
Glass
25x50 mL bottles | 0019-1333-06
12x100 mL bottles | 0019-1333-11
12x150 mL bottles | 0019-1333-16
12x200 mL fill/250 mL bottles | 0019-1333-21
Plastic
20x50 mL hand held syringes | 0019-1333-78
20x75 mL fill/125 mL power injector syringes | 0019-1333-95
20x100 mL fill/125 mL power injector syringes | 0019-1333-90
20x125 mL power injector syringes | 0019-1333-87
RFID-Tagged Syringes*
20x100 mL fill/125 mL power injector syringes | 0019-1333-00
20x125 mL power injector syringes | 0019-1333-27
OPTIRAY 320
Glass
25x20 mL vials | 0019-1323-02
25x50 mL bottles | 0019-1323-06
12x100 mL bottles | 0019-1323-11
12x150 mL bottles | 0019-1323-16
12x200 mL fill/250 mL bottles | 0019-1323-21
Plastic
20x50 mL hand held syringes | 0019-1323-78
20x50 mL fill/125 mL power injector syringes | 0019-1323-52
20x75 mL fill/125 mL power injector syringes | 0019-1323-95
20x100 mL fill/125 mL power injector syringes | 0019-1323-90
20x125 mL power injector syringes | 0019-1323-87
RFID-Tagged Syringes*
20x75 mL fill/125 mL power injector syringes | 0019-1323-85
20x100 mL fill/125 mL power injector syringes | 0019-1323-00
20x125 mL power injector syringes | 0019-1323-27
OPTIRAY 300
Glass
25x50 mL bottles | 0019-1332-06
12x100 mL bottles | 0019-1332-11
12x150 mL bottles | 0019-1332-16
12x200 mL fill/250 mL bottles | 0019-1332-21
Plastic
20x100 mL fill/125 mL power injector syringes | 0019-1332-90
RFID-Tagged Syringes*
20x100 mL fill/125 mL power injector syringes | 0019-1332-00

*Radio Frequency Identification (RFID) Technology

RFID-Tagged Syringe Description
This information is for UltrajectTM syringes containing OPTIRAY that have been labeled with a Radio Frequency Identification (RFID) tag. When used with an RFID-enabled OptivantageTM injector, this tag allows for the exchange of product information such as lot number, expiration, concentration, and identification of the syringe as being “unused” prior to use and “used” after product administrations. Patient information is not used in any form with this RFID technology. OPTIRAY product quality is not influenced by the use of this RFID tag.

RFID-Tagged Syringe Directions for Use
For the RFID Technology to function, the syringe must be used with an Optivantage Injector with RFID technology [see Dosage and Administration (2.2)]. Function of the RFID technology is not dependent on syringe orientation as it is placed in the injector. Instructions for use of injector are provided on the injector interface screen and operator’s manual.

If the RFID tag is damaged or otherwise non-functional, the injector will notify the user. Should this occur the OPTIRAY syringe with the non-functional RFID tag may still be used but no data will be transferred to the injector.

Regarding interference with medical devices, the RFID tag and injector system meet the IEC 60601-1-2 requirements for emission and immunity standards for medical devices. Follow all manufacturers’ guidelines and do not operate any part of the Optivantage Injector System and RFID-tagged syringes within 6 inches (15 cm) of a pacemaker and/or defibrillator.

16.2 Storage

- Store at 25°C (77°F); excursions permitted to 15° to 30°C (59° to 86°F).
- Protect from strong daylight or direct exposure to the sun.
- Store up to 40°C (104°F) for up to one month in a contrast media warmer utilizing circulating warm air.
- May store OPTIRAY for periods longer than one month.
- Store OPTIRAY RFID-tagged syringes at the same conditions listed for the drug product.
- Discard OPTIRAY syringes, glass bottles, and their contents if they are frozen or if crystallization occurs.

16.3 Handling

- Do not re-autoclave plastic container because of possible damage to syringe.
- RFID-tagged syringes require no special handling.

17 PATIENT COUNSELING INFORMATION

Hypersensitivity Reactions
Advise the patient concerning the risk of hypersensitivity reactions that can occur both during and after OPTIRAY administration. Advise the patient to report any signs or symptoms of hypersensitivity reactions during the procedure and to seek medical attention for signs or symptoms experienced after discharge [see Warnings and Precautions (5.2)].

Advise patients to inform their physician if they develop a rash after receiving OPTIRAY [see Warnings and Precautions (5.10)].

Contrast Induced Acute Kidney Injury
Advise the patient concerning appropriate hydration to decrease the risk of contrast induced kidney injury [see Warnings and Precautions (5.3)].

Extravasation
If extravasation occurs during injection, advise patients to seek medical care for progression of symptoms [see Warnings and Precautions (5.6)].

Thyroid Dysfunction
Advise parents/caregivers about the risk of developing thyroid dysfunction after OPTIRAY administration. Advise parents/caregivers about when to seek medical care for their child to monitor for thyroid function [see Warnings and Precautions (5.8)].

Manufactured by:
Liebel-Flarsheim Company LLC
Raleigh, NC 27616

Made in USA

GBT 1323C0223

PACKAGE LABEL - PRINCIPAL DISPLAY PANEL - Optiray 350, Ioversol Injection 74%

Single Dose Container 50 mL

Sterile Solution NDC 0019-1333-78

Optiray® 350

Ioversol Injection 74%

350 mg/mL Organically Bound Iodine

For Intravenous and Intra-arterial Use Only Rx only

Not For Intrathecal Use

Medication and fuid pathway are sterile. Outside of syringe is not sterile.
Single dose syringe • Discard unused portion and syringe.
Protect from light • Store at 25°C (77°F); excursions permitted to 15° to 30°C (59° to 86°F) [see USP Controlled Room Temperature].
Each mL contains 741 mg ioversol, 3.6 mg tromethamine as a bufer and 0.2 mg edetate calcium disodium as a stabilizer. The pH is adjusted with hydrochloric acid or sodium hydroxide.
Discard contents if syringe is frozen, if crystallization occurs, syringe seal is broken or if leaking is observed.
Recommended Dosage: See Prescribing Information for indications, dosage and dispensing information.

Manufactured by:
Liebel-Flarsheim Company LLC
Raleigh, NC 27616 Made in USA

Single Dose Container 75 mL
Sterile Solution NDC 0019-1333-95
Optiray® 350

Ioversol Injection 74%

350 mg/mL Organically Bound Iodine

For Intravenous and Intra-arterial Use Only Rx only

Not For Intrathecal Use

Medication and fuid pathway are sterile.
Outside of syringe is not sterile.
Single dose syringe • Discard unused portion and syringe.
Protect from light • Store at 25°C (77°F); excursions permitted to 15° to 30°C (59° to 86°F) [see USP Controlled Room Temperature].
Each mL contains 741 mg ioversol, 3.6 mg tromethamine as a bufer and 0.2 mg edetate calcium disodium as a stabilizer.
The pH is adjusted with hydrochloric acid or sodium hydroxide.
Discard contents if syringe is frozen, if crystallization occurs, syringe seal is broken or if leaking is observed.
Recommended Dosage: See Prescribing Information for indications, dosage and dispensing information.

Manufactured by:
Liebel-Flarsheim Company LLC
Raleigh, NC 27616 Made in USA

Single Dose Container 100 mL
Sterile Solution NDC 0019-1333-90
Optiray® 350

Ioversol Injection 74%

350 mg/mL Organically Bound Iodine

For Intravenous and Intra-arterial Use Only Rx only

Not For Intrathecal Use

Medication and fuid pathway are sterile. Outside of syringe is not sterile.
Single dose syringe • Discard unused portion and syringe.
Protect from light • Store at 25°C (77°F); excursions permitted to 15° to 30°C (59° to 86°F) [see USP Controlled Room Temperature].
Each mL contains 741 mg ioversol, 3.6 mg tromethamine as a bufer and 0.2 mg edetate calcium disodium as a stabilizer. The pH is adjusted with hydrochloric acid or sodium hydroxide.
Discard contents if syringe is frozen, if crystallization occurs, syringe seal is broken or if leaking is observed.
Recommended Dosage: See Prescribing Information for indications, dosage and dispensing information.

Manufactured by:
Liebel-Flarsheim Company LLC
Raleigh, NC 27616 Made in USA

Single Dose Container 125 mL
Sterile Solution NDC 0019-1333-87
Optiray® 350

Ioversol Injection 74%
350 mg/mL Organically Bound Iodine
For Intravenous and Intra-arterial Use Only Rx only
Not For Intrathecal Use
Medication and fuid pathway are sterile. Outside of syringe is not sterile.
Single dose syringe • Discard unused portion and syringe.
Protect from light • Store at 25°C (77°F); excursions permitted to 15° to 30°C (59° to 86°F) [see USP Controlled Room Temperature].
Each mL contains 741 mg ioversol, 3.6 mg tromethamine as a bufer and 0.2 mg edetate calcium disodium as a stabilizer. The pH is adjusted with hydrochloric acid or sodium hydroxide.
Discard contents if syringe is frozen, if crystallization occurs, syringe seal is broken or if leaking is observed.
Recommended Dosage: See Prescribing Information for indications, dosage and dispensing information.
Manufactured by:
Liebel-Flarsheim Company LLC
Raleigh, NC 27616
Made in USA

PACKAGE LABEL - PRINCIPAL DISPLAY PANEL - Optiray 320, Ioversol Injection 68%

Single Dose Container 50 mL
Sterile Solution NDC 0019-1323-78

Optiray® 320

Ioversol Injection 68%

320 mg/mL Organically Bound Iodine

For Intravenous and Intra-arterial Use Only Rx only

Not For Intrathecal Use

Medication and fuid pathway are sterile. Outside of syringe is not sterile.
Single dose syringe • Discard unused portion and syringe.
Protect from light • Store at 25°C (77°F); excursions permitted to 15° to 30°C (59° to 86°F) [see USP Controlled Room Temperature].
Each mL contains 678 mg ioversol, 3.6 mg tromethamine as a bufer and 0.2 mg edetate calcium disodium as a stabilizer. The pH is adjusted with hydrochloric acid or sodium hydroxide.
Discard contents if syringe is frozen, if crystallization occurs, syringe seal is broken or if leaking is observed.
Recommended Dosage: See Prescribing Information for indications, dosage and dispensing information.

Manufactured by:
Liebel-Flarsheim Company LLC
Raleigh, NC 27616 Made in USA

Single Dose Container 50 mL
Sterile Solution NDC 0019-1323-52

Optiray® 320
Ioversol Injection 68%

320 mg/mL Organically Bound Iodine
For Intravenous and Intra-arterial Use Only Rx only

Not For Intrathecal Use

Medication and fuid pathway are sterile.
Outside of syringe is not sterile.
Single dose syringe • Discard unused portion and syringe.
Protect from light • Store at 25°C (77°F); excursions permitted to 15° to 30°C (59° to 86°F) [see USP Controlled Room Temperature].
Each mL contains 678 mg ioversol, 3.6 mg tromethamine as a bufer and 0.2 mg edetate calcium disodium as a stabilizer.
The pH is adjusted with hydrochloric acid or sodium hydroxide.
Discard contents if syringe is frozen, if crystallization occurs, syringe seal is broken or if leaking is observed.
Recommended Dosage: See Prescribing Information for indications, dosage and dispensing information.

Manufactured by:
Liebel-Flarsheim Company LLC
Raleigh, NC 27616 Made in USA

Single Dose Container 75 mL
Sterile Solution NDC 0019-1323-95
Optiray® 320
Ioversol Injection 68%

320 mg/mL Organically Bound Iodine

For Intravenous and Intra-arterial Use Only Rx only

Not For Intrathecal Use

Medication and fuid pathway are sterile.
Outside of syringe is not sterile.
Single dose syringe • Discard unused portion and syringe.
Protect from light • Store at 25°C (77°F); excursions permitted to 15° to 30°C (59° to 86°F) [see USP Controlled Room Temperature].
Each mL contains 678 mg ioversol, 3.6 mg tromethamine as a bufer and 0.2 mg edetate calcium disodium as a stabilizer.
The pH is adjusted with hydrochloric acid or sodium hydroxide.
Discard contents if syringe is frozen, if crystallization occurs, syringe seal is broken or if leaking is observed.
Recommended Dosage: See Prescribing Information for indications, dosage and dispensing information.

Manufactured by:
Liebel-Flarsheim Company LLC
Raleigh, NC 27616 Made in USA

Single Dose Container 100 mL
Sterile Solution NDC 0019-1323-90
Optiray® 320
Ioversol Injection 68%

320 mg/mL Organically Bound Iodine

For Intravenous and Intra-arterial Use Only Rx only

Not For Intrathecal Use

Medication and fuid pathway are sterile. Outside of syringe is not sterile.
Single dose syringe • Discard unused portion and syringe.
Protect from light • Store at 25°C (77°F); excursions permitted to 15° to 30°C (59° to 86°F) [see USP Controlled Room Temperature].
Each mL contains 678 mg ioversol, 3.6 mg tromethamine as a bufer and 0.2 mg edetate calcium disodium as a stabilizer. The pH is adjusted with hydrochloric acid or sodium hydroxide.
Discard contents if syringe is frozen, if crystallization occurs, syringe seal is broken or if leaking is observed.
Recommended Dosage: See Prescribing Information for indications, dosage and dispensing information.

Manufactured by:
Liebel-Flarsheim Company LLC
Raleigh, NC 27616 Made in USA

Single Dose Container 125 mL
Sterile Solution NDC 0019-1323-87
Optiray® 320

Ioversol Injection 68%

320 mg/mL Organically Bound Iodine

For Intravenous and Intra-arterial Use Only Rx only

Not For Intrathecal Use

Medication and fuid pathway are sterile. Outside of syringe is not sterile.
Single dose syringe • Discard unused portion and syringe.
Protect from light • Store at 25°C (77°F); excursions permitted to 15° to 30°C (59° to 86°F) [see USP Controlled Room Temperature].
Each mL contains 678 mg ioversol, 3.6 mg tromethamine as a bufer and 0.2 mg edetate calcium disodium as a stabilizer. The pH is adjusted with hydrochloric acid or sodium hydroxide.
Discard contents if syringe is frozen, if crystallization occurs, syringe seal is broken or if leaking is observed.
Recommended Dosage: See Prescribing Information for indications, dosage and dispensing information.

Manufactured by:
Liebel-Flarsheim Company LLC
Raleigh, NC 27616 Made in USA

PACKAGE LABEL - PRINCIPAL DISPLAY PANEL - Optiray 300, Ioversol Injection 64%

Single Dose Container 100 mL
Sterile Solution NDC 0019-1332-90

Optiray® 300
Ioversol Injection 64%

300 mg/mL Organically Bound Iodine

For Intravenous and Intra-arterial Use Only Rx only

Not For Intrathecal Use

Medication and fuid pathway are sterile. Outside of syringe is not sterile.
Single dose syringe • Discard unused portion and syringe.
Protect from light • Store at 25°C (77°F); excursions permitted to 15° to 30°C (59° to 86°F) [see USP Controlled Room Temperature].
Each mL contains 636 mg ioversol, 3.6 mg tromethamine as a bufer and 0.2 mg edetate calcium disodium as a stabilizer. The pH is adjusted with hydrochloric acid or sodium hydroxide.
Discard contents if syringe is frozen, if crystallization occurs, syringe seal is broken or if leaking is observed.
Recommended Dosage: See Prescribing Information for indications, dosage and dispensing information.

Manufactured by:
Liebel-Flarsheim Company LLC
Raleigh, NC 27616 Made in USA